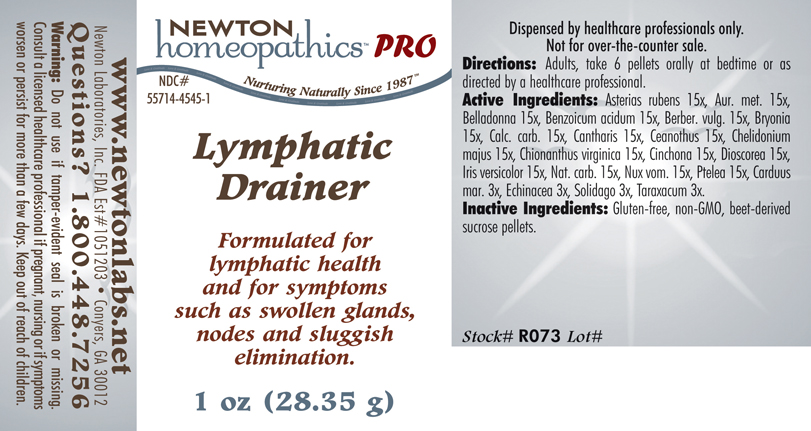 DRUG LABEL: Lymphatic Drainer 
NDC: 55714-4545 | Form: PELLET
Manufacturer: Newton Laboratories, Inc.
Category: homeopathic | Type: HUMAN PRESCRIPTION DRUG LABEL
Date: 20110601

ACTIVE INGREDIENTS: Asterias Rubens 15 [hp_X]/1 g; Gold 15 [hp_X]/1 g; Atropa Belladonna 15 [hp_X]/1 g; Benzoic Acid 15 [hp_X]/1 g; Berberis Vulgaris Root Bark 15 [hp_X]/1 g; Bryonia Alba Root 15 [hp_X]/1 g; Oyster Shell Calcium Carbonate, Crude 15 [hp_X]/1 g; Lytta Vesicatoria 15 [hp_X]/1 g; Ceanothus Americanus Leaf 15 [hp_X]/1 g; Chelidonium Majus 15 [hp_X]/1 g; Cinchona Officinalis Bark 15 [hp_X]/1 g; Chionanthus Virginicus Bark 15 [hp_X]/1 g; Dioscorea Villosa Tuber 15 [hp_X]/1 g; Iris Versicolor Root 15 [hp_X]/1 g; Sodium Carbonate 15 [hp_X]/1 g; Strychnos Nux-vomica Seed 15 [hp_X]/1 g; Ptelea Trifoliata Bark 15 [hp_X]/1 g; Silybum Marianum Seed 3 [hp_X]/1 g; Echinacea, Unspecified 3 [hp_X]/1 g; Solidago Virgaurea Flowering Top 3 [hp_X]/1 g; Taraxacum Officinale 3 [hp_X]/1 g
INACTIVE INGREDIENTS: Sucrose

Lymphatic Drainer

INDICATIONS & USAGE SECTION

Lymphatic Drainer Formulated for lymphatic health and for symptoms such as swollen glands, nodes and sluggish elimination.

DOSAGE & ADMINISTRATION SECTION

Directions: Adults, take 6 pellets orally at bedtime or as directed by a healthcare professional.

ACTIVE INGREDIENT SECTION

Asterias rubens 15x, Aur. met. 15x, Belladonna 15x, Benzoicum acidum 15x, Berber. vulg. 15x, Bryonia 15x, Calc. carb. 15x, Cantharis 15x, Ceanothus 15x, Chelidonium majus 15x, Chionanthus virginica 15x, Cinchona 15x, Dioscorea 15x, Iris versicolor 15x, Nat. carb. 15x, Nux vom. 15x, Ptelea 15x, Carduus mar. 3x, Echinacea 3x, Solidago 3x, Taraxacum 3x.

PURPOSE SECTION

Formulated for lymphatic health and for symptoms such as swollen glands, nodes and sluggish elimination.

INACTIVE INGREDIENT SECTION

Inactive Ingredients: Gluten-free, non-GMO, beet-derived sucrose pellets.

QUESTIONS? SECTION

www.newtonlabs.net Newton Laboratories, Inc. FDA Est # 1051203 - Conyers, GA 30012
Questions? 1.800.448.7256

WARNINGS SECTION

Warning: Do not use if tamper - evident seal is broken or missing. Consult a licensed healthcare professional if pregnant, nursing or if symptoms worsen or persist for more than a few days. Keep out of reach of children.

PREGNANCY OR BREAST FEEDING SECTION

Consult a licensed healthcare professional if pregnant, nursing or if symptoms worsen or persist for more than a few days.

KEEP OUT OF REACH OF CHILDREN SECTION

Keep out of reach of children.